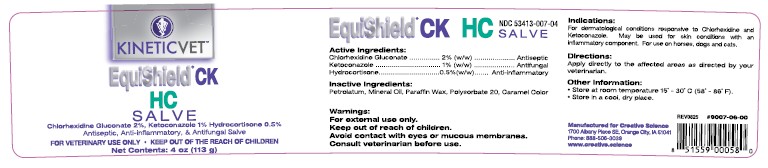 DRUG LABEL: EquiShield CK HC
NDC: 53413-007 | Form: SALVE
Manufacturer: Creative Science
Category: animal | Type: OTC ANIMAL DRUG LABEL
Date: 20251206

ACTIVE INGREDIENTS: CHLORHEXIDINE GLUCONATE 2 g/100 g; KETOCONAZOLE 1 g/100 g; HYDROCORTISONE 0.5 g/100 g

EquiShield CK HC Salve

NDC 53413-007-04

Active Ingredients:

Chlorhexidine Gluconate .......... 2% (w/w) ................. Antiseptic
Ketoconazole .......................... 1% (w/w) .................Antifungal
Hydrocortisone ......................0.5% (w/w) ......Anti-inflammatory

Inactive Ingredients:

Petrolatum, Mineral Oil, Paraffin Was, Polysorbate 20, Caramel Color

Warnings:

For external use only.

Keep out of reach of children.

Avoid contact with eyes or mucous membranes.

Consult veterinarian before use.

Indications:

For dermatological conditions responsive to Chlorhexidine and Ketoconazole. May be used for skin conditions with an inflammatory component. For use on horses, dogs and cats.

Directions:

Apply directly to the affected areas as directed by your veterinarian.

Other Information:

• Store at room temperature 15˚ - 30˚C (58˚ - 86˚F).
• Store in a cool, dry place.

Rev 0825 #9007-06-00
UPC 851559000580

Manufactured for Creative Science

1700 Albany Place SE, Orange City, IA 51041

Phone: 888-506-3039

www.creative.science

KINETICVET™

EquiShield® CK HC SALVE

Chlorhexidine Gluconate 2%, Ketoconazole 1%, Hydrocortisone 0.5%

Antiseptic & Anti-inflammatory, & Antifungal Salve

FOR VETERINARY USE ONLY • KEEP OUT OF THE REACH OF CHILDREN

Net Contents: 4 oz (113 g)